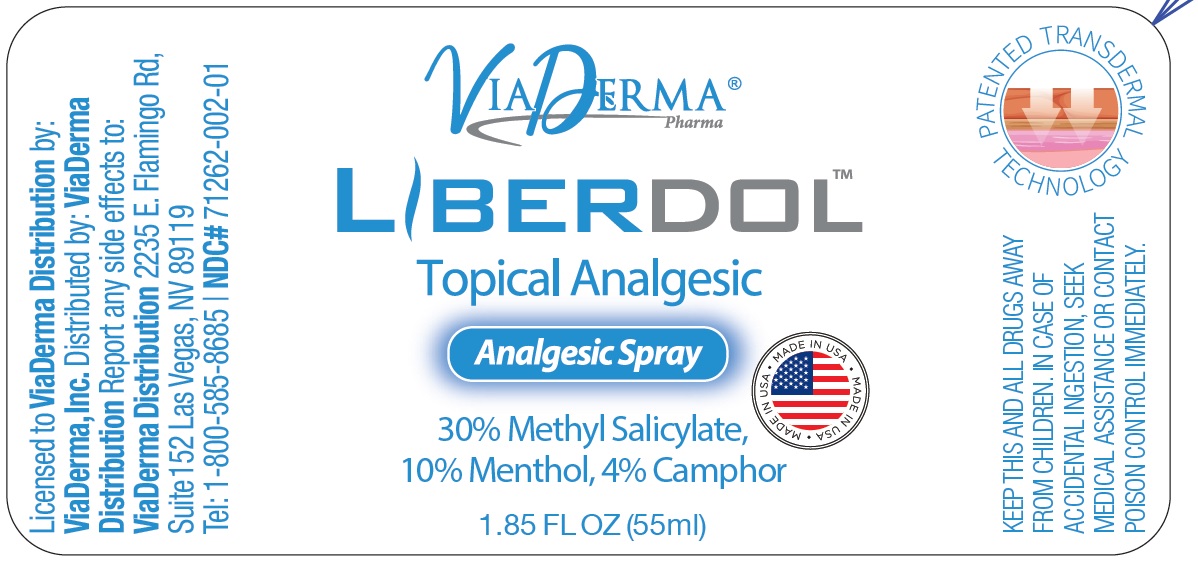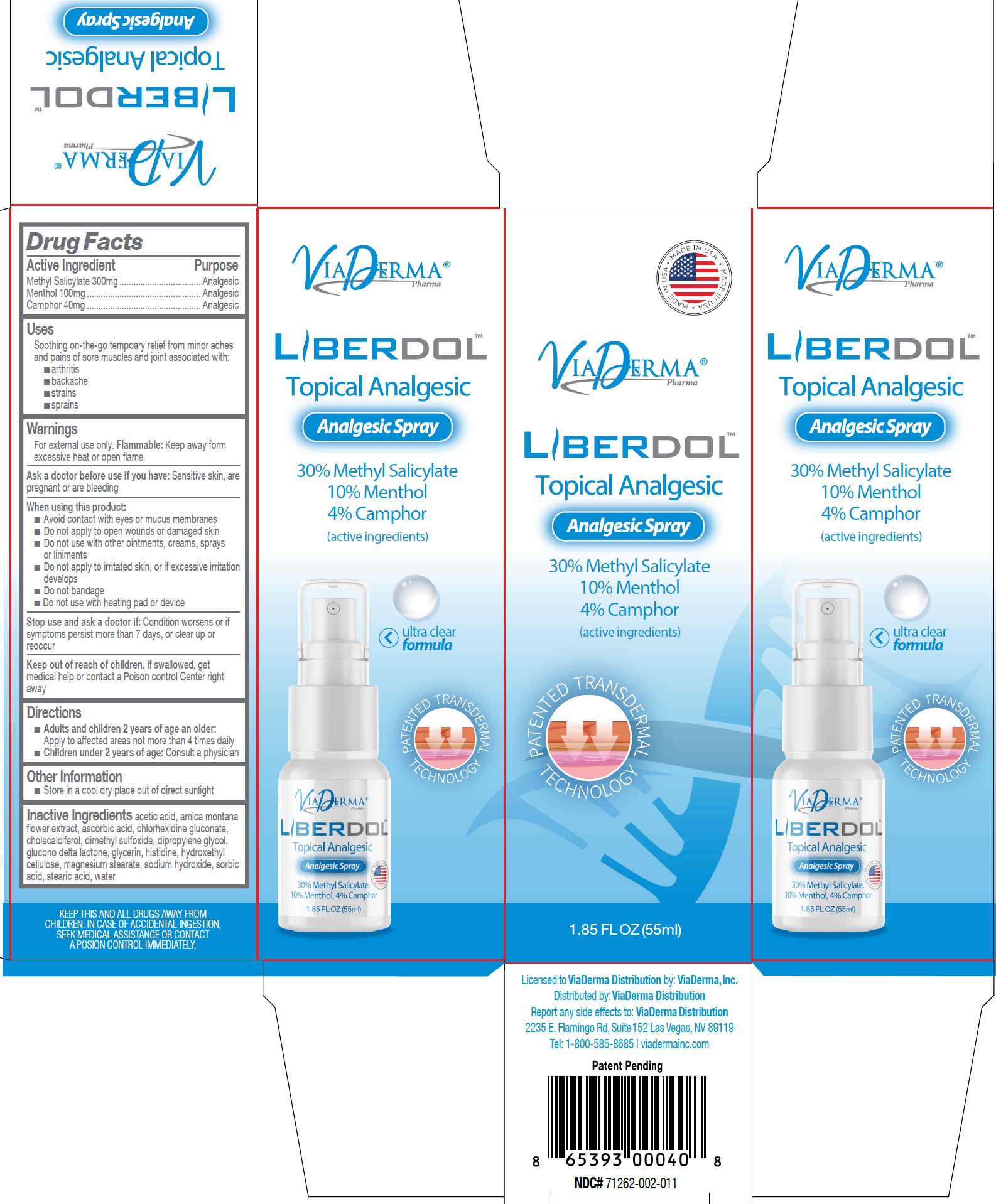 DRUG LABEL: Liberdol Topical Analgesic
NDC: 71262-008 | Form: SPRAY
Manufacturer: ViaDerma Distribution, Inc
Category: otc | Type: HUMAN OTC DRUG LABEL
Date: 20231201

ACTIVE INGREDIENTS: METHYL SALICYLATE 300 mg/1 mL; MENTHOL 100 mg/1 mL; CAMPHOR (SYNTHETIC) 40 mg/1 mL
INACTIVE INGREDIENTS: ACETIC ACID; ARNICA MONTANA FLOWER; ASCORBIC ACID; CHLORHEXIDINE GLUCONATE; CHOLECALCIFEROL; DIMETHYL SULFOXIDE; DIPROPYLENE GLYCOL; GLUCONOLACTONE; GLYCERIN; HISTIDINE; HYDROXYETHYL CELLULOSE, UNSPECIFIED; MAGNESIUM STEARATE; SODIUM HYDROXIDE; SORBIC ACID; STEARIC ACID; WATER

Liberdol Topical Analgesic Spray

Active Ingredient

Methyl Salicylate 300mg

Menthol 100mg

Camphor 40mg

Purpose

Analgesic

Uses

Soothing on-the-go tempoary relief from minor aches and pains of sore muscles and joint associated with:

- arthritis
- backache
- strains
- sprains

Warnings

For external use only. : Keep away form excessive heat or open flame Flammable

Ask a doctor before use if you have:

Sensitive skin, are pregnant or are bleeding

When using this product:

- Avoid contact with eyes or mucus membranes
- Do not apply to open wounds or damaged skin
- Do not use with other ointments, creams, sprays or liniments
- Do not apply to irritated skin, or if excessive irritation develops
- Do not bandage
- Do not use with heating pad or device

Stop use and ask a doctor if:

Condition worsens or if symptoms persist more than 7 days, or clear up or reoccur

Keep out of reach of children.

If swallowed, get medical help or contact a Poison control Center right away

Directions

- Apply to affected areas not more than 4 times daily Adults and children 2 years of age an older:
- Consult a physician Children under 2 years of age:

Other Information

- Store in a cool dry place out of direct sunlight

Inactive Ingredients

acetic acid, arnica montana flower extract, ascorbic acid, chlorhexidine gluconate, cholecalciferol, dimethyl sulfoxide, dipropylene glycol, glucono delta lactone, glycerin, histidine, hydroxethyl cellulose, magnesium stearate, sodium hydroxide, sorbic acid, stearic acid, water